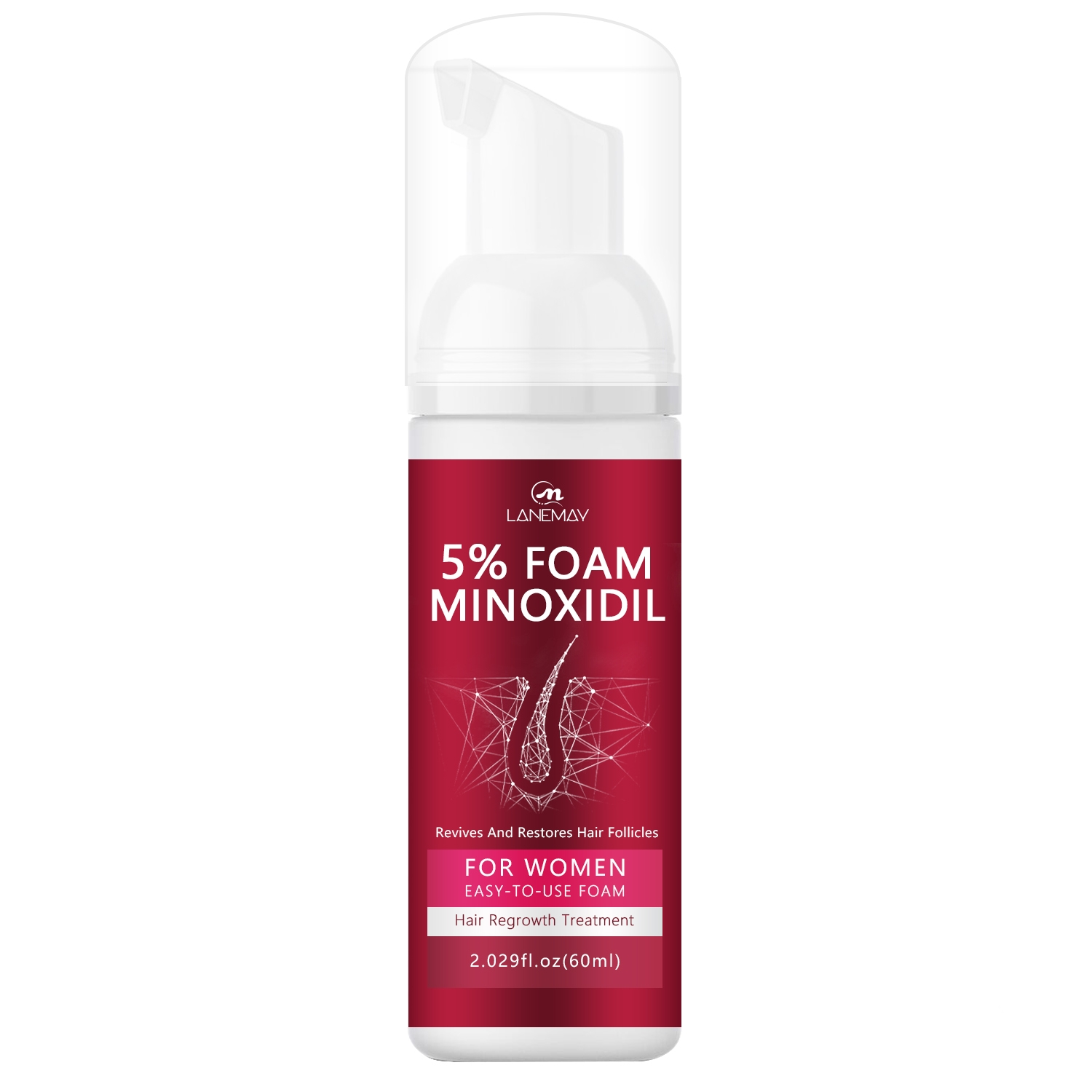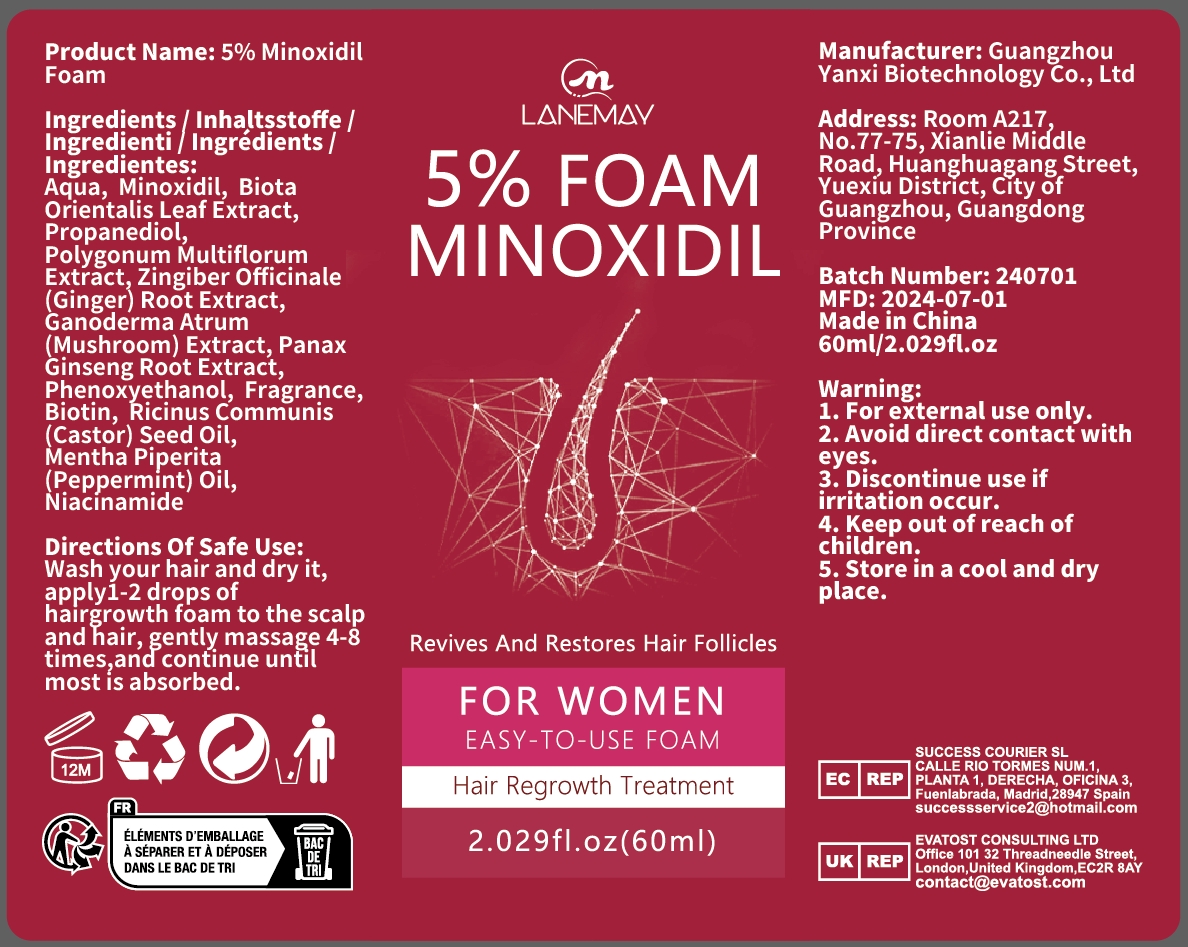 DRUG LABEL: 5% Minoxidil Foam
NDC: 84025-180 | Form: LIQUID
Manufacturer: Guangzhou Yanxi Biotechnology Co.. Ltd
Category: otc | Type: HUMAN OTC DRUG LABEL
Date: 20240904

ACTIVE INGREDIENTS: PROPANEDIOL 5 mg/30 mL; MINOXIDIL 3 mg/30 mL
INACTIVE INGREDIENTS: WATER

WARNINGS

keep out of children

INACTIVE INGREDIENT

AQUA

DOSAGE AND ADMINISTRATION

Hair growth solution for treating female hair loss

INDICATIONS AND USAGE

For daily skin care

keep out of children

PURPOSE

Effectively relieve female hair loss and keep hair growing healthily